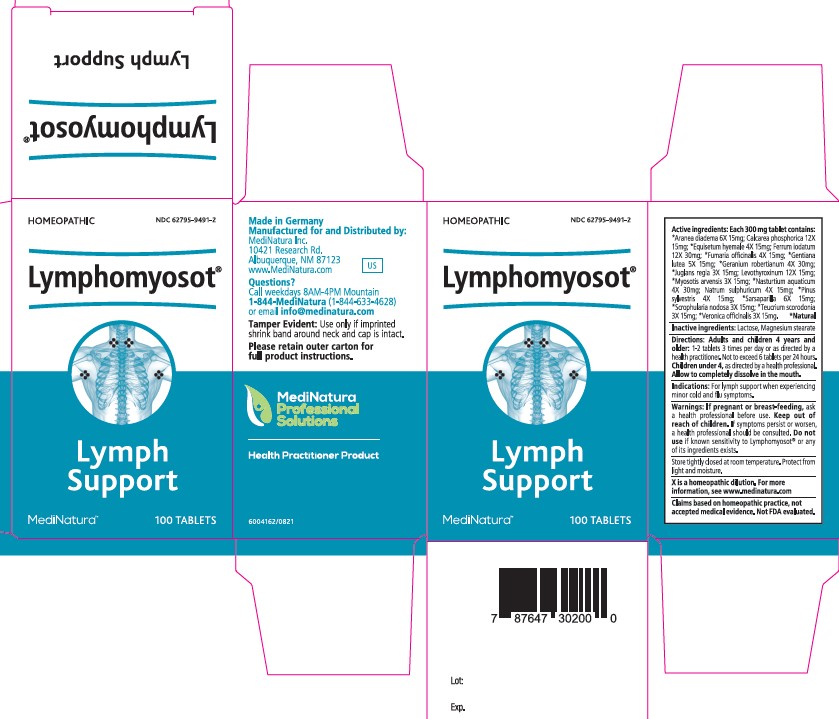 DRUG LABEL: Lymphomyosot
NDC: 62795-9491 | Form: TABLET
Manufacturer: MediNatura Inc
Category: homeopathic | Type: HUMAN OTC DRUG LABEL
Date: 20230510

ACTIVE INGREDIENTS: ARANEUS DIADEMATUS 6 [hp_X]/1 1; TRIBASIC CALCIUM PHOSPHATE 12 [hp_X]/1 1; EQUISETUM HYEMALE WHOLE 4 [hp_X]/1 1; FERROUS IODIDE 12 [hp_X]/1 1; FUMARIA OFFICINALIS FLOWERING TOP 4 [hp_X]/1 1; GENTIANA LUTEA ROOT 5 [hp_X]/1 1; GERANIUM ROBERTIANUM 4 [hp_X]/1 1; JUGLANS REGIA LEAF 3 [hp_X]/1 1; LEVOTHYROXINE SODIUM ANHYDROUS 12 [hp_X]/1 1; MYOSOTIS ARVENSIS WHOLE 3 [hp_X]/1 1; NASTURTIUM OFFICINALE 4 [hp_X]/1 1; SODIUM SULFATE 4 [hp_X]/1 1; PINUS SYLVESTRIS LEAFY TWIG 4 [hp_X]/1 1; SMILAX ORNATA ROOT 6 [hp_X]/1 1; SCROPHULARIA NODOSA WHOLE 3 [hp_X]/1 1; TEUCRIUM SCORODONIA FLOWERING TOP 3 [hp_X]/1 1; VERONICA OFFICINALIS FLOWERING TOP 3 [hp_X]/1 1
INACTIVE INGREDIENTS: LACTOSE, UNSPECIFIED FORM; MAGNESIUM STEARATE

Lymphomyosot

Warnings:

If pregnant or breast-feeding, ask
a health professional before use. Keep out of
reach of children. If symptoms persist or worsen,
a health professional should be consulted. Do not
use if known sensitivity to Lymphomyosot® or any
of its ingredients exists.

KEEP OUT OF REACH OF CHILDREN

Purpose

Lymph
Support

Active ingredients:

Each 300 mg tablet contains:
*Aranea diadema 6X 15mg; Calcarea phosphorica 12X
15mg; *Equisetum hyemale 4X 15mg; Ferrum iodatum
12X 30mg; *Fumaria officinalis 4X 15mg; *Gentiana
lutea 5X 15mg; *Geranium robertianum 4X 30mg;
*Juglans regia 3X 15mg; Levothyroxinum 12X 15mg;
*Myosotis arvensis 3X 15mg; *Nasturtium aquaticum
4X 30mg; Natrum sulphuricum 4X 15mg; *Pinus
sylvestris 4X 15mg; *Sarsaparilla 6X 15mg;
*Scrophularia nodosa 3X 15mg; *Teucrium scorodonia
3X 15mg; *Veronica officinalis 3X 15mg. *Natural

Inactive ingredients:

Lactose, Magnesium stearate

Directions

Adults and children 4 years and
older: 1-2 tablets 3 times per day or as directed by a
health practitioner. Not to exceed 6 tablets per 24
hours. Children under 4, as directed by a health
professional. Allow to completely dissolve in the mouth.

Indications:

For lymph support when experiencing
minor cold and flu symptoms.